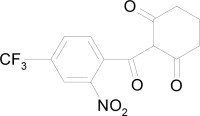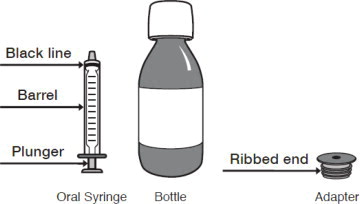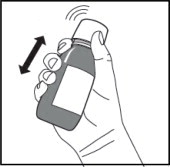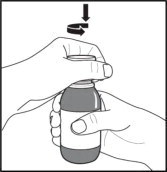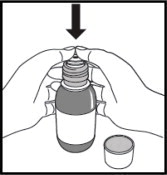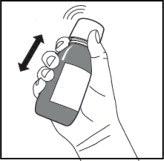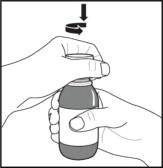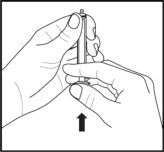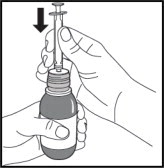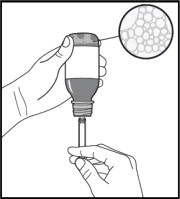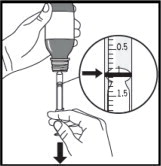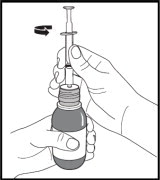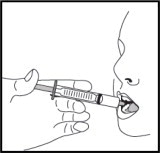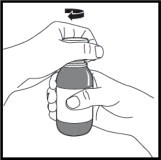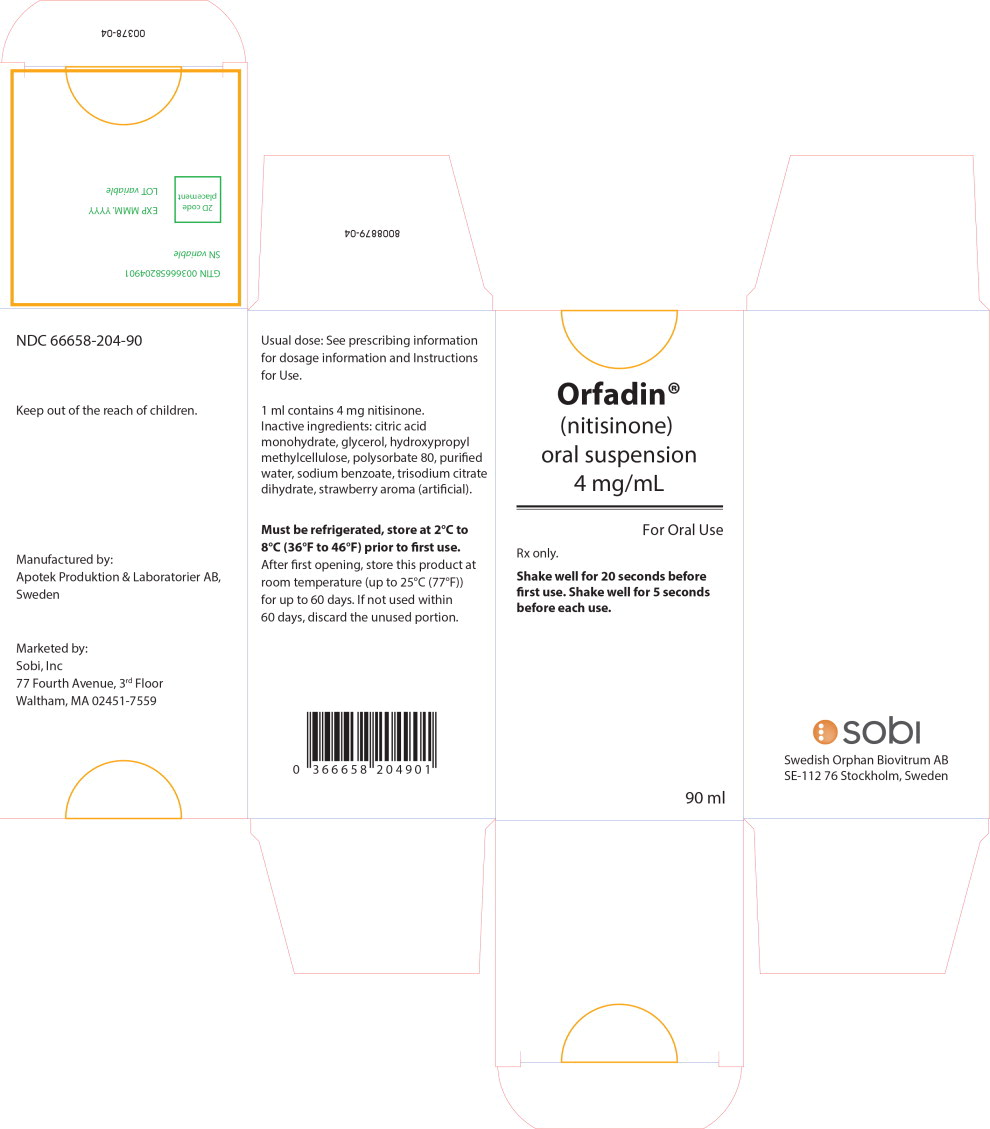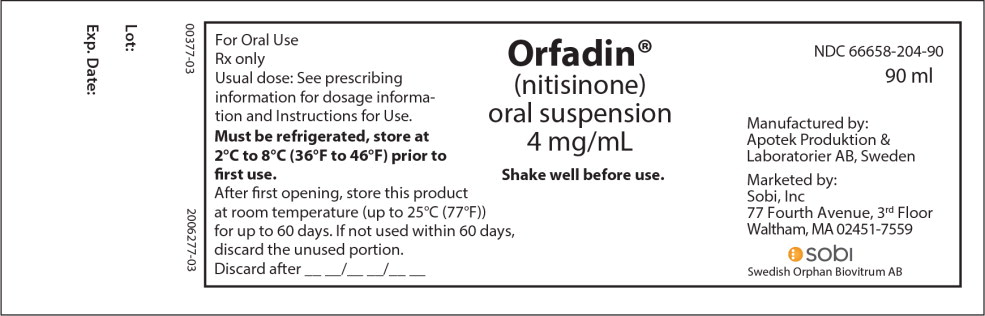 DRUG LABEL: ORFADIN
NDC: 66658-204 | Form: SUSPENSION
Manufacturer: Swedish Orphan Biovitrum AB (publ)
Category: prescription | Type: HUMAN PRESCRIPTION DRUG LABEL
Date: 20251218

ACTIVE INGREDIENTS: NITISINONE 4 mg/1 mL
INACTIVE INGREDIENTS: HYPROMELLOSES; GLYCERIN; POLYSORBATE 80; SODIUM BENZOATE; CITRIC ACID MONOHYDRATE; TRISODIUM CITRATE DIHYDRATE; WATER

HIGHLIGHTS OF PRESCRIBING INFORMATION

These highlights do not include all the information needed to use ORFADIN safely and effectively. See full prescribing information for ORFADIN.
ORFADIN®(nitisinone) capsules, for oral use
ORFADIN®(nitisinone) oral suspension
Initial U.S. Approval: 2002

RECENT MAJOR CHANGES

Warnings and Precautions (5.1) | 05/2019

1 INDICATIONS AND USAGE

ORFADIN is a hydroxy-phenylpyruvate dioxygenase inhibitor indicated for the treatment of adult and pediatric patients with hereditary tyrosinemia type 1 (HT-1) in combination with dietary restriction of tyrosine and phenylalanine. (1)

2 DOSAGE AND ADMINISTRATION

Recommended Dosage (2.1) :

- The recommended starting dosage is 0.5 mg/kg orally twice daily.
- In patients 5 years of age and older who have undetectable serum and urine succinylacetone concentrations after a minimum of 4 weeks on a stable dosage of nitisinone, the total daily dose may be given once daily.
- Titrate the dosage based on biochemical and/or clinical response, as described in the full prescribing information.
- The maximum total daily dosage is 2 mg/kg orally.

Preparation and Administration Instructions (2.2) :

- For instructions on preparing, measuring and administering the oral suspension, see the full prescribing information.
- Maintain dietary restriction of tyrosine and phenylalanine
- Take ORFADIN capsules at least one hour before, or two hours after a meal
- For patients who have difficulties swallowing capsules and who are intolerant to the oral suspension, the capsules may be opened and the contents suspended in a small amount of water, formula or apple sauce immediately before use.

Take ORFADIN oral suspension without regard to meals.

3 DOSAGE FORMS AND STRENGTHS

- Capsules: 2 mg, 5 mg, 10 mg, 20 mg. (3)
- Oral suspension: 4 mg/mL (3)

4 CONTRAINDICATIONS

None (4)

5 WARNINGS AND PRECAUTIONS

- Elevated Plasma Tyrosine Levels, Ocular Symptoms, Developmental Delay and Hyperkeratotic Plaques: Inadequate restriction of tyrosine and phenylalanine intake can lead to elevations in plasma tyrosine, which at levels above 500 micromol/L can result in symptoms, intellectual disability and developmental delay or painful hyperkeratotic plaques on the soles and palms; do not adjust ORFADIN dosage in order to lower the plasma tyrosine concentration. Obtain slit-lamp examination prior to treatment, regularly during treatment; Reexamine patients if symptoms develop or tyrosine levels are > 500 micromol/L. Assess plasma tyrosine levels in patients with an abrupt change in neurologic status. (5.1)
- Leukopenia and Severe Thrombocytopenia: Monitor platelet and white blood cell counts. (5.2)
- Risk of Adverse Reactions Due to Glycerol Content of ORFADIN Oral Suspension: Doses of 20 mL of ORFADIN oral suspension may cause headache, upset stomach and diarrhea due to the glycerol content. Consider switching patients to ORFADIN capsules. (5.3)

6 ADVERSE REACTIONS

Most common adverse reactions (>1%) are elevated tyrosine levels, thrombocytopenia, leukopenia, conjunctivitis, corneal opacity, keratitis, photophobia, eye pain, blepharitis, cataracts, granulocytopenia, epistaxis, pruritus, exfoliative dermatitis, dry skin, maculopapular rash and alopecia. (6.1)

To report SUSPECTED ADVERSE REACTIONS, contact Swedish Orphan Biovitrum at 1-866-773-5274 or FDA at 1-800-FDA-1088 or www.fda.gov/medwatch.

7 DRUG INTERACTIONS

- CYP2C9 Substrates: Increased systemic exposure of these co-administered drugs; reduce the dosage. Additional dosage adjustments may be needed to maintain therapeutic drug concentrations for narrow therapeutic index drugs. (7)
- OAT1/OAT3 Substrates: Increased systemic exposure of these co-administered drugs; monitor for potential adverse reactions. (7)

FULL PRESCRIBING INFORMATION

1 INDICATIONS AND USAGE

ORFADIN®is indicated for the treatment of adult and pediatric patients with hereditary tyrosinemia type 1 (HT-1) in combination with dietary restriction of tyrosine and phenylalanine.

2 DOSAGE AND ADMINISTRATION

2.1 Dosage

Starting Dosage

The recommended starting dosage of ORFADIN is 0.5 mg/kg administered orally twice daily.

Maintenance Regimen

In patients 5 years of age and older who have undetectable serum and urine succinylacetone concentrations after a minimum of 4 weeks on a stable dosage of nitisinone, the total daily dose of ORFADIN may be given once daily (e.g., 1 to 2 mg/kg once daily) [see Clinical Pharmacology (12.2)] .

Dosage Titration

Titrate the dosage in each individual patient based on biochemical and/or clinical response.

- Monitor plasma and/or urine succinylacetone concentrations, liver function parameters and alpha-fetoprotein levels.
- If succinylacetone is still detectable in blood or urine 4 weeks after the start of nitisinone treatment, increase the nitisinone dosage to 0.75 mg/kg twice daily. A maximum total daily dosage of 2 mg/kg may be needed based on the evaluation of all biochemical parameters.
- If the biochemical response is satisfactory (undetectable blood and/or urine succinylacetone), the dosage should be adjusted only according to body weight gain and not according to plasma tyrosine levels.
- During initiation of therapy, when switching from twice daily to once daily dosing, or if there is a deterioration in the patient's condition, it may be necessary to follow all available biochemical parameters more closely (i.e. plasma and/or urine succinylacetone, urine 5-aminolevulinate (ALA) and erythrocyte porphobilinogen (PBG)-synthase activity).
- Maintain plasma tyrosine levels below 500 micromol/L by dietary restriction of tyrosine and phenylalanine intake [see Warnings and Precautions (5.1)] . In patients who develop plasma tyrosine levels above 500 micromol/L, assess dietary tyrosine and phenylalanine intake. Do not adjust the ORFADIN dosage in order to lower the plasma tyrosine concentration.

2.2 Preparation and Administration Instructions

Preparation of the Oral Suspension

The oral suspension will be dispensed with an oral syringe of appropriate size and a bottle adaptor provided by a pharmacist or other healthcare provider.

Preparing a Bottle Without the Adapter Already Inserted:

- Store the bottle in the refrigerator prior to first use.
- Remove the bottle from the refrigerator. Calculate 60 days from when the bottle is removed from the refrigerator. Write this date as the “Discard after” date on the bottle label.
- Allow the bottle to warm to room temperature (30 to 60 minutes).
- Shake the bottle vigorously for at least 20 seconds until the solid cake at the bottom of the bottle is completely dispersed. Check that there are no particles left at the bottom of the bottle. Foam will form in the bottle.
- Insert the bottle adapter.

Preparing a Bottle With the Adapter Inserted:

- Shake the bottle vigorously for at least 5 seconds. Check that there are no particles left at the bottom of the bottle. Foam will form in the bottle.

Measuring and Administering the Dose

Once the bottle is prepared with the adapter:

1. Use the oral syringe to measure the dose.
2. Keep the bottle upright and insert the oral syringe into the adapter.
3. Carefully turn the bottle upside down with the oral syringe in place. Wait for the foam to rise to the top of the bottle.
4. Pull back on the syringe plunger to withdraw the dose.
5. Leave the syringe in the adapter and turn the bottle upright.
6. Remove the syringe from the adapter by gently twisting it out of the bottle.
7. Dispense the dose into the patient's mouth.
8. Do not remove the bottle adapter.
9. Store the bottle at room temperature (not above 25°C).

Administration of ORFADIN Capsules and Oral Suspension

- Maintain dietary restriction of tyrosine and phenylalanine when taking ORFADIN.
- Capsules:Take at least one hour before, or two hours after a meal [see Clinical Pharmacology (12.3)] . For patients who have difficulty swallowing the capsules and who are intolerant to the oral suspension [see Warnings and Precautions (5.3)] , the capsules may be opened and the contents suspended in a small amount of water, formula or apple sauce immediately before use.
- Oral suspension:Take without regard to meals [see Clinical Pharmacology (12.3)] .

3 DOSAGE FORMS AND STRENGTHS

- Capsules: 2 mg, 5 mg, 10 mg and 20 mg white capsules imprinted with “NTBC” followed by “2 mg”, “5 mg”, “10 mg” or ”20 mg”, indicating the actual amount of nitisinone in each capsule.
- Oral suspension: 4 mg/mL, a white, slightly viscous opaque suspension.

4 CONTRAINDICATIONS

None.

5 WARNINGS AND PRECAUTIONS

5.1 Elevated Plasma Tyrosine Levels, Ocular Symptoms, Developmental Delay and Hyperkeratotic Plaques

Nitisinone is an inhibitor of 4-hydroxyphenyl-pyruvate dioxygenase, an enzyme in the tyrosine metabolic pathway [see Clinical Pharmacology (12.1)] . Therefore, treatment with ORFADIN may cause an increase in plasma tyrosine levels in patients with HT-1. Maintain concomitant reduction in dietary tyrosine and phenylalanine while on ORFADIN treatment. Do not adjust ORFADIN dosage in order to lower the plasma tyrosine concentration. Maintain plasma tyrosine levels below 500 micromol/L. Inadequate restriction of tyrosine and phenylalanine intake can lead to elevations in plasma tyrosine levels and levels greater than 500 micromol/L may lead to the following:

- Ocular signs and symptoms including corneal ulcers, corneal opacities, keratitis, conjunctivitis, eye pain, and photophobia have been reported in patients treated with ORFADIN [see Adverse Reactions (6.1)] . In a clinical study in a non HT-1 population without dietary restriction and reported tyrosine levels >500 micromol/L both symptomatic and asymptomatic keratopathies have been observed. Therefore, perform a baseline ophthalmologic examination including slit-lamp examination prior to initiating ORFADIN treatment and regularly thereafter. Patients who develop photophobia, eye pain, or signs of inflammation such as redness, swelling, or burning of the eyes or tyrosine levels are > 500 micromol/L during treatment with ORFADIN should undergo slit-lamp reexamination and immediate measurement of the plasma tyrosine concentration.
- Variable degrees of intellectual disability and developmental delay. In patients treated with ORFADIN who exhibit an abrupt change in neurologic status, perform a clinical laboratory assessment including plasma tyrosine levels.
- Painful hyperkeratotic plaques on the soles and palms

In patients with HT-1 treated with dietary restrictions and ORFADIN who develop elevated plasma tyrosine levels, assess dietary tyrosine and phenylalanine intake.

5.2 Leukopenia and Severe Thrombocytopenia

In clinical trials, patients treated with ORFADIN and dietary restriction developed transient leukopenia (3%), thrombocytopenia (3%), or both (1.5%) [see Adverse Reactions (6.1)] . No patients developed infections or bleeding as a result of the episodes of leukopenia and thrombocytopenia. Monitor platelet and white blood cell counts during ORFADIN therapy.

5.3 Risk of Adverse Reactions Due to Glycerol Content of ORFADIN Oral Suspension

Oral doses of glycerol of 10 grams or more have been reported to cause headache, upset stomach and diarrhea. ORFADIN oral suspension contains 500 mg/mL of glycerol. Patients receiving more than 20 mL of ORFADIN oral suspension (10 grams glycerol) as a single dose are at increased risk of these adverse reactions. Consider switching patients who are unable to tolerate the oral suspension to ORFADIN capsules.

6 ADVERSE REACTIONS

6.1 Clinical Trials Experience

Because clinical trials are conducted under widely varying conditions, adverse reaction rates observed in the clinical trials of a drug cannot be directly compared to rates in the clinical trials of another drug and may not reflect the rates observed in clinical practice.

ORFADIN was studied in one open-label, uncontrolled study of 207 patients with HT-1, ages 0 to 22 years at enrollment (median age 9 months), who were diagnosed with HT-1 by the presence of succinylacetone in the urine or plasma. The starting dose of ORFADIN was 0.3 to 0.5 mg/kg twice daily, and the dose was increased in some patients to 1 mg/kg twice daily based on weight, biochemical, and enzyme markers. The recommended starting dosage of ORFADIN is 0.5 mg/kg twice daily [see Dosage and Administration (2.1)] . Median duration of treatment was 22 months (range 0.1 to 80 months).

The most serious adverse reactions reported during ORFADIN treatment were thrombocytopenia, leukopenia, porphyria, and ocular/visual complaints associated with elevated tyrosine levels [see Warnings and Precautions (5.1, 5.2)] . Fourteen patients experienced ocular/visual events. The duration of the symptoms varied from 5 days to 2 years. Six patients had thrombocytopenia, three of which had platelet counts 30,000/microL or lower. In 4 patients with thrombocytopenia, platelet counts gradually returned to normal (duration up to 47 days) without change in ORFADIN dose. No patients developed infections or bleeding as a result of the episodes of leukopenia and thrombocytopenia.

Patients with HT- 1 are at increased risk of developing porphyric crises, hepatic neoplasms, and liver failure requiring liver transplantation. These complications of HT-1 were observed in patients treated with nitisinone for a median of 22 months during the clinical trial (liver transplantation 13%, liver failure 7%, malignant hepatic neoplasms 5%, benign hepatic neoplasms 3%, porphyria 1%).

The most common adverse reactions reported in the clinical trial are summarized in Table 1.

TABLE 1
Most Common Adverse Reactions in Patients with HT-1 Treated with Nitisinone*
Elevated tyrosine levels Leukopenia Thrombocytopenia Conjunctivitis Corneal opacity Keratitis Photophobia Eye pain Blepharitis Cataracts Granulocytopenia Epistaxis Pruritus Exfoliative dermatitis Dry skin Maculopapular rash Alopecia | >10% 3% 3% 2% 2% 2% 2% 1% 1% 1% 1% 1% 1% 1% 1% 1% 1%
*reported in at least 1% of patients

Adverse reactions reported in less than 1% of the patients, included death, seizure, brain tumor, encephalopathy, hyperkinesia, cyanosis, abdominal pain, diarrhea, enanthema, gastrointestinal hemorrhage, melena, elevated hepatic enzymes, liver enlargement, hypoglycemia, septicemia, and bronchitis.

7 DRUG INTERACTIONS

Nitisinone is a moderate CYP2C9 inhibitor, a weak CYP2E1 inducer and an inhibitor of OAT1/OAT3. Table 2includes drugs with clinically important drug interactions when administered concomitantly with ORFADIN and instructions for preventing or managing them.

Table 2: Clinically Relevant Interactions Affecting Co-Administered Drugs
Sensitive CYP2C9 Substrates (e.g., celecoxib, tolbutamide) or CYP2C9 Substrates with a Narrow Therapeutic Index (e.g., phenytoin, warfarin)
Clinical Impact | Increased exposure of the co-administered drugs metabolized by CYP2C9. [see Clinical Pharmacology (12.3)]
Intervention | Reduce the dosage of the co-administered drugs metabolized by CYP2C9 drug by half. Additional dosage adjustments may be needed to maintain therapeutic drug concentrations for narrow therapeutic index drugs. See prescribing information for those drugs.
OAT1/OAT3 Substrates (e.g., adefovir, ganciclovir, methotrexate)
Clinical Impact | Increased exposure of the interacting drug [see Clinical Pharmacology (12.3)]
Intervention | Monitor for potential adverse reactions related to the co-administered drug.

8 USE IN SPECIFIC POPULATIONS

8.1 Pregnancy

Risk Summary

Limited available data with nitisinone use in pregnant women are not sufficient to determine a drug-associated risk of adverse developmental outcomes. Animal reproduction studies have been conducted for nitisinone. In these studies, nitisinone was administered to mice and rabbits during organogenesis with oral doses of nitisinone up to 20 and 8 times respectively, the recommended initial dose of 1 mg/kg/day. In mice, nitisinone caused incomplete skeletal ossification of fetal bones and decreased pup survival at doses 0.4 times the recommended initial dose, and increased gestational length at doses 4 times the recommended initial dose. In rabbits, nitisinone caused maternal toxicity and incomplete skeletal ossification of fetal bones at doses 1.6 times the recommended initial dose [see Data] .

The background risk of major birth defects and miscarriage for the indicated population are unknown. In the U.S. general population, the estimated background risk of major birth defects and miscarriage in clinically recognized pregnancies is 2 to 4% and 15 to 20%, respectively.

Data

Animal Data

Reproduction studies have been performed in mice at oral doses of about 0.4, 4 and 20 times the recommended initial dose (1 mg/kg/day) and in rabbits at oral doses of about 1.6, 4 and 8 times the recommended initial dose based on the body surface area. In mice, nitisinone has been shown to cause incomplete skeletal ossification of fetal bones at 0.4, 4 and 20 times the recommended initial dose, increased gestational length at 4 and 20 times the recommended initial dose, and decreased pup survival at 0.4 times the recommended initial dose based on the body surface area. In rabbits, nitisinone caused incomplete skeletal ossification of fetal bones at 1.6, 4 and 8 times the recommended initial dose based on the body surface area.

8.2 Lactation

Risk Summary

There are no data on the presence of nitisinone in human milk, the effects on the breastfed infant, or the effects on milk production. Data suggest that nitisinone is present in rat milk due to findings of ocular toxicity and lower body weight seen in drug naive nursing rat pups. The development and health benefits of breastfeeding should be considered along with the mother's clinical need for ORFADIN and any potential adverse effects on the breastfed infant from ORFADIN or from the underlying maternal condition.

8.4 Pediatric Use

The safety and effectiveness of ORFADIN have been established in pediatric patients for the treatment of HT-1 in combination with dietary restriction of tyrosine and phenylalanine. Use of ORFADIN in pediatric patients is supported by evidence from one open-label, uncontrolled clinical study conducted in 207 patients with HT-1 ages 0 to 22 years (median age 9 months) [see Clinical Studies (14)] .

8.5 Geriatric Use

Clinical studies of nitisinone did not include any subjects aged 65 and over. No pharmacokinetic studies of nitisinone have been performed in geriatric patients. In general, dose selection for an elderly patient should be cautious reflecting the greater frequency of decreased hepatic, renal, or cardiac function, and concomitant disease or other drug therapy in this patient population.

10 OVERDOSAGE

Accidental ingestion of ORFADIN by individuals eating normal diets not restricted in tyrosine and phenylalanine will result in elevated tyrosine levels. In healthy subjects given a single 1 mg/kg dose of nitisinone, the plasma tyrosine level reached a maximum of 1200 micromol/L at 48 to 120 hours after dosing. After a washout period of 14 days, the mean value of plasma tyrosine was still 808 micromol/L. Fasted follow-up samples obtained from volunteers several weeks later showed tyrosine values back to normal. There were no reports of changes in vital signs or laboratory data of any clinical significance. One patient reported sensitivity to sunlight. Hyper-tyrosinemia has been reported with ORFADIN treatment [see Warnings and Precautions (5.1)] .

11 DESCRIPTION

ORFADIN contains nitisinone, which is a hydroxyphenyl-pyruvate dioxygenase inhibitor indicated as an adjunct to dietary restriction of tyrosine and phenylalanine in the treatment of hereditary tyrosinemia type 1 (HT-1).

Nitisinone occurs as white to yellowish-white, crystalline powder. It is practically insoluble in water, soluble in 2M sodium hydroxide and in methanol, and sparingly soluble in alcohol.

Chemically, nitisinone is 2-(2-nitro-4-trifluoromethylbenzoyl) cyclohexane-1,3-dione, and the structural formula is:

Capsules: Hard, white-opaque capsule, marked as 2 mg, 5 mg, 10 mg or 20 mg strengths of nitisinone, intended for oral administration. Each capsule contains 2 mg, 5 mg, 10 mg or 20 mg nitisinone, plus pre-gelatinized starch. The capsule shell is gelatin and titanium dioxide and the imprint is an iron oxide.

Oral suspension: 4 mg/mL, a white, slightly viscous opaque suspension. The inactive ingredients are hydroxypropyl methylcellulose, glycerol, polysorbate 80, sodium benzoate, citric acid monohydrate, trisodium citrate dihydrate, strawberry aroma (artificial) and purified water.

Glycerol: Each mL contains 500 mg.

Sodium: Each mL contains 0.7 mg (0.03 mEq).

12 CLINICAL PHARMACOLOGY

12.1 Mechanism of Action

Nitisinone is a competitive inhibitor of 4-hydroxyphenyl-pyruvate dioxygenase, an enzyme upstream of fumarylacetoacetate hydrolase (FAH) in the tyrosine catabolic pathway. By inhibiting the normal catabolism of tyrosine in patients with HT-1, nitisinone prevents the accumulation of the catabolic intermediates maleylacetoacetate and fumarylacetoacetate. In patients with HT-1, these catabolic intermediates are converted to the toxic metabolites succinylacetone and succinylacetoacetate, which are responsible for the observed liver and kidney toxicity. Succinylacetone can also inhibit the porphyrin synthesis pathway leading to the accumulation of 5-aminolevulinate, a neurotoxin responsible for the porphyric crises characteristic of HT-1.

12.2 Pharmacodynamics

In a clinical study, patients with HT-1 were diagnosed by the presence of succinylacetone in urine or plasma and treated with ORFADIN [see Clinical Studies (14)] . In all 186 patients whose urine succinylacetone was measured, the urinary succinylacetone concentration decreased to less than 1 mmol/mol creatinine, the lower limit of quantitation. The median time to normalization of urine succinylacetone was 0.3 months. The probability of recurrence of abnormal values of urine succinylacetone was 1% at a nitisinone concentration of 37 micromol/L (95% confidence interval: 23, 51 micromol/L). In 87% (150/172) of patients whose plasma succinylacetone was measured, the plasma succinylacetone concentration decreased to less than 0.1 micromol/L, the lower limit of quantitation. The median time to normalization of plasma succinylacetone was 3.9 months.

In another study, comparing two dosing regimens, succinylacetone was measured in urine and/or blood in 16 patients with HT-1 aged 5 years to 24 years. All study patients were on a stable ORFADIN daily dosage (0.4 mg/kg/day to 1 mg/kg/day) during both study dosing regimens. After at least 4 weeks of twice daily dosing with ORFADIN, both the urine and/or blood succinylacetone concentrations were below the limit of quantitation for the assay. Patients were then switched to once daily dosing with the same total daily dosage of ORFADIN and blood and/or urine succinylacetone concentrations remained undetectable when measured following at least 4 weeks of treatment with once daily dosing.

Nitisinone inhibits catabolism of the amino acid tyrosine and can result in elevated plasma levels of tyrosine. Therefore, treatment with nitisinone requires restriction of the dietary intake of tyrosine and phenylalanine to prevent the toxicity associated with elevated plasma levels of tyrosine [see Warnings and Precautions (5.1)].

12.3 Pharmacokinetics

The single-dose pharmacokinetics of nitisinone have been studied for both ORFADIN capsules and ORFADIN oral suspension in healthy adult subjects and the multiple-dose pharmacokinetics have been studied for ORFADIN capsules in healthy subjects.

Absorption

The pharmacokinetic characteristics following single oral administration of ORFADIN 30 mg under fasting conditions are shown in Table 3. Compared to ORFADIN capsule, the median Tmaxoccurred about 3 hours earlier with ORFADIN oral suspension. The multiple-dose characteristics of ORFADIN 80 mg once daily are shown in Table 4. Steady-state (SS) was reached within 14 days dosing in all subjects.

TABLE 3 Nitisinone Arithmetic Mean (CV%) Pharmacokinetic Parameters in Healthy Subjects Following a Single Oral 30 mg Dose of ORFADIN Under Fasting Conditions
Treatment | Cmax (micromol/L) [range] | tmax* (h) [range] | AUC 0-72h (micromol·h/L) [range]
ORFADIN capsule (n=12) | 10.5 (26) | 3.5 | 406 (13)
 |  | [0.8 to 8.0]
ORFADIN oral suspension (n=12) | 10.1 (34) | 0.4 | 350 (17)
 |  | [0.2 to 4.0]
* presented as median [range]

TABLE 4 Nitisinone Arithmetic Mean (CV%) Pharmacokinetic Parameters in Healthy Subjects Following Repeated Once Daily Administration of 80 mg ORFADIN Under Fasting Conditions.
Treatment | Cmax,ss (micromol/L) [CV%] | Cmin,ss (micromol/L) [range] | tmax,ss* (h) [range] | AUC 0-24h,ss (micromol·h/L) [range]
ORFADIN capsule (n=18) | 120 (23) | 73(24) | 4.0 | 2204(18)
 |  |  | [0.0 to 16.0]
* presented as median [range]

Food Effect:No food effect study was conducted with ORFADIN capsules. For ORFADIN oral suspension, a high calorie (800 to 1000 calories) and high fat meal (approximately 50% of total caloric content) did not affect nitisinone total exposure (AUC72h), but decreased the Cmaxby approximately 20% [see Dosage and Administration (2.2)] .

Distribution

In vitrobinding of nitisinone to human plasma proteins is greater than 95% at 50 micromolar concentration.

Elimination

The mean terminal plasma half-life of single dose nitisinone in healthy male subjects is 54 hours. The mean (CV%)apparent plasma clearance in 18 healthy adults following multiple once daily doses of ORFADIN 80 mg is 113 (16) mL/h.

Metabolism: In vitrostudies have shown that nitisinone is relatively stable in human liver microsomes with minor metabolism possibly mediated by CYP3A4 enzyme.

Excretion:Renal elimination of nitisinone is of minor importance, since the mean of the fraction of dose excreted as unchanged nitisinone in the urine (fe(%)) was 3.0% (n=3) following multiple oral doses of 80 mg daily in healthy subjects. The estimated mean (CV%) renal clearance of nitisinone was 0.003 L/h (25%).

Drug Interaction Studies

Nitisinone does not inhibit CYP2D6. Nitisinone is a moderate inhibitor of CYP2C9, and a weak inducer of CYP2E1 (Table 5). Nitisinone is an inhibitor of OAT1/3 (Table 5).

Table 5. Percent Change in AUC0-∞and Cmaxfor Co-administered Drugs in the Presence of ORFADIN in 18 Healthy Subjects
Co-administered Druga | Dose of Co-administered Drug (Route of Administration) | Effect of Nitisinone on the Pharmacokinetics of Co-administered Drugb
Co-administered Druga | Dose of Co-administered Drug (Route of Administration) | AUC 0-∞ | Cmax
CYP2C9 Substrate Tolbutamidec | 500 mg (oral) | 131% ↑ | 16% ↑
CYP2E1 Substrate Chlorzoxazone | 250 mg (oral) | 27% ↓ | 18% ↓
OAT1/3 Substrate Furosemide | 20 mg (intravenous) | 72% ↑ | 12% ↑
↑ = Increased; ↓ = Decreased
aThe interacting drug was administered alone on Day 1 and together with ORFADIN on Day 17.
bMultiple doses of 80 mg ORFADIN were administered daily alone from Day 3 to Day 16.
c16 subjects in Period 2 received ORFADIN and tolbutamide while 18 subjects in Period 1 received ORFADIN alone.

In Vitro Studies Where Drug Interaction Potential Was Not Further Evaluated Clinically

In vitrostudies showed that nitisinone does not inhibit CYP1A2, 2C19, or 3A4. Nitisinone does not induce CYP1A2, 2B6 or 3A4/5. Nitisinone does not inhibit P-gp, BCRP, OATP1B1, OATP1B3 and OCT2-mediated transports at therapeutically relevant concentrations.

13 NONCLINICAL TOXICOLOGY

13.1 Carcinogenesis, Mutagenesis, Impairment of Fertility

The carcinogenic potential of nitisinone was assessed in a 26-week oral (gavage) carcinogenicity study in Tg.rasH2 mice. There were no drug-related neoplastic findings in male or female Tg.rasH2 mice at doses up to 100 mg/kg/ day nitisinone (approximately 8.1 times the recommended initial dose of 1 mg/kg/day on a body surface area basis).

Nitisinone was not genotoxic in the Ames test and the in vivomouse liver unscheduled DNA synthesis (UDS) test. Nitisinone was mutagenic in the mouse lymphoma cell (L5178Y/TK+/-) forward mutation test and in an in vivomouse bone marrow micronucleus test.

In a single dose-group study in rats given 100 mg/kg (16.2 times the recommended initial dose of 1 mg/kg/day on a body surface area basis), reduced litter size, decreased pup weight at birth, and decreased survival of pups after birth was demonstrated.

14 CLINICAL STUDIES

The efficacy and safety of ORFADIN in patients with HT-1 was evaluated in one open-label, uncontrolled study of 207 patients with HT-1, ages 0 to 22 years at enrollment (median age 9 months). Patients were diagnosed with HT-1 by the presence of succinylacetone in the urine or plasma. All patients were treated with ORFADIN at a starting dose of 0.3 to 0.5 mg/kg twice daily, and the dose was increased in some patients to 1 mg/kg twice daily based on weight, liver and kidney function tests, platelet count, serum amino acids, urinary phenolic acid, plasma and urine succinylacetone, erythrocyte PBG-synthase, and urine 5-ALA. The median duration of treatment was 22 months (range less than 1 month to 80 months). Efficacy was assessed by comparison of survival and incidence of liver transplant to historical controls.

For patients presenting with HT-1 younger than 2 months of age who were treated with dietary restriction and nitisinone, 2- and 4-year survival probabilities were 88% and 88%, respectively. Data from historical controls showed that patients presenting with HT-1 at younger than 2 months of age and treated with dietary restriction alone had 2- and 4-year survival probabilities of 29% and 29%, respectively. For patients presenting with HT-1 between 2 months and 6 months of age who were treated with dietary restriction and nitisinone, 2- and 4-year survival probabilities were 94% and 94%, respectively. Data for historical controls showed that patients presenting with HT-1 between 2 months and 6 months of age treated with dietary restriction alone had 2- and 4-year survival probabilities of 74% and 60%, respectively.

The effects of nitisinone on urine and plasma succinylacetone, porphyrin metabolism, and urinary alpha-1-microglobulin were also assessed in this clinical study.

Porphyria-like crisis were reported in 3 patients (0.3% of cases per year) during the clinical study. This compares to an incidence of 5 to 20% of cases per year expected as part of the natural history of the disorder. An assessment of porphyria-like crises was performed because these events are commonly reported in patients with HT-1 who are not treated with nitisinone.

Urinary alpha-1-microglobulin, a proposed marker of proximal tubular dysfunction, was measured in 100 patients at baseline. The overall median pretreatment level was 4.3 grams/mol creatinine. After one year of treatment in a subgroup of patients (N=100), overall median alpha-1-microglobulin decreased by 1.5 grams/mol creatinine. In patients 24 months of age and younger in whom multiple values were available (N=65), median alpha-1-microglobulin levels decreased from 5.0 to 3.0 grams/mol creatinine (reference value for age less than or equal to 12 grams/mol creatinine). In patients older than 24 months in whom multiple values were available (N=35), median alpha-1-microglobulin levels decreased from 2.8 to 2.0 grams/mol creatinine (reference for age less than or equal to 6 grams/mol creatinine).

The long term effect of nitisinone on hepatic function was not assessed.

16 HOW SUPPLIED/STORAGE AND HANDLING

Capsules: White capsules marked in black with "NTBC" and identified as 2 mg, 5 mg, 10 mg or 20 mg strengths of nitisinone. The capsules are packed in a high density (HD) polyethylene container with a tamper-resistant low density (LD) polyethylene snap-on cap. Each bottle contains 60 capsules.

- 2 mg white capsules imprinted "NTBC 2 mg" in black ink, NDC 66658-102-60
- 5 mg white capsules imprinted "NTBC 5 mg" in black ink, NDC 66658-105-60
- 10 mg white capsules imprinted "NTBC 10 mg" in black ink, NDC 66658-110-60
- 20 mg white capsules imprinted "NTBC 20 mg" in black ink, NDC 66658-120-60
- Store refrigerated at 2° to 8°C (36° to 46°F). Alternatively, patients/caregivers may store ORFADIN capsules at room temperature up to 25°C (77°F) for up to 45 days. If not used within 45 days, discard ORFADIN capsules.

Oral suspension: White, slightly viscous opaque suspension. 1 mL contains 4 mg of nitisinone. The suspension is provided in a 100 mL brown bottle (type III glass) with a white child resistant HDPE screw cap with sealing and tamper evidence. Each bottle contains 90 mL oral suspension.

- Oral suspension 4 mg/mL, NDC 66658-204-90
- Store refrigerated at 2°C to 8°C (36°F to 46°F) prior to first use. Do not freeze. Store upright.
- After first opening, store the product at room temperature (up to 25°C (77°F)) for up to 60 days. If not used within 60 days, discard unused portion. The discard after date should be noted on the bottle

17 PATIENT COUNSELING INFORMATION

Advise the patient to read the FDA-approved patient labeling (Instructions for Use).

Preparation and Administration Instructions [see Dosage and Administration (2.2)]

Preparation of the Oral Suspension

The oral suspension will be dispensed with an oral syringe of appropriate size and a bottle adaptor provided by a pharmacist or other healthcare provider.

Preparing a Bottle Without the Adapter Already Inserted:

- Store the bottle in the refrigerator prior to first use.
- Remove the bottle from the refrigerator. Calculate 60 days from when the bottle is removed from the refrigerator. Write this date as the “Discard after” date on the bottle label.
- Allow the bottle to warm to room temperature (30 to 60 minutes).
- Shake the bottle vigorously for at least 20 seconds until the solid cake at the bottom of the bottle is completely dispersed. Check that there are no particles left at the bottom of the bottle. Foam will form in the bottle.
- Insert the bottle adapter.

Preparing a Bottle With the Adapter Inserted:

- Shake the bottle vigorously for at least 5 seconds. Check that there are no particles left at the bottom of the bottle. Foam will form in the bottle.

Measuring and Administering the Dose

Once the bottle is prepared with the adapter:

1. Use the oral syringe to measure the dose.
2. Keep the bottle upright and insert the oral syringe into the adapter.
3. Carefully turn the bottle upside down with the oral syringe in place. Wait for the foam to rise to the top of the bottle.
4. Pull back on the syringe plunger to withdraw the dose.
5. Leave the syringe in the adapter and turn the bottle upright.
6. Remove the syringe from the adapter by gently twisting it out of the bottle.
7. Dispense the dose into the patient's mouth.
8. Do not remove the bottle adapter.
9. Store the bottle at room temperature (not above 25°C).

Administration of ORFADIN Capsules and Oral Suspension

- Maintain dietary restriction of tyrosine and phenylalanine when taking ORFADIN.
- Capsules:Take at least one hour before, or two hours after a meal. For patients who have difficulty swallowing the capsules and for which the oral suspension is not suitable [see Warnings and Precautions (5.3]) , the capsules may be opened and the contents suspended in a small amount of water, formula or apple sauce immediately before use. Or, the oral suspension may be used instead.
- Oral suspension:Take without regard to meals.

Elevated Plasma Tyrosine Levels, Ocular Symptoms, Developmental Delay and Hyperkeratotic Plaques

- Inform patients that inadequate restriction may be associated with ocular signs and symptoms, intellectual disability and developmental delay, and painful hyperkeratotic plaques on the soles and palms. Advise patients and caregivers of the need to maintain dietary restriction of tyrosine and phenylalanine and to report any unexplained ocular, neurologic, or other symptoms promptly to their healthcare provider [see Warnings and Precautions (5.1)].

Risk of Adverse Reactions Due to Glycerol Content of ORFADIN Oral Suspension

Advise patients receiving doses of greater than 20 mL of ORFADIN oral suspension that they may experience headache, upset stomach and diarrhea due to the glycerol component of the formulation and if they develop symptoms to report these to their healthcare provider [see Warnings and Precautions (5.3)].

Manufactured by:
Apotek Produktion & Laboratorier AB, Sweden

Marketed by:
Sobi, Inc
77 Fourth Avenue, 3rdFloor, Waltham, MA 02451-7559

Instructions for Use

ORFADIN (OR-fuh-din)

(nitisinone)

oral suspension

4 mg/mL

Read this Instructions for Use before you start taking ORFADIN oral suspension and each time you get a refill. There may be new information. This information does not take the place of talking to your healthcare provider about your medical condition or your treatment.

Important information about measuring ORFADIN oral suspension:

- Use the oral syringe provided with your ORFADIN oral suspension to make sure you measure the right amount.
- You will be provided with:
  - 1 bottle of ORFADIN oral suspension
  - 1 oral syringe
  - 1 adapter (The adapter may or may not be inserted in your bottle of ORFADIN oral suspension when you receive it.)

Figure A

If the adapter is notinserted in your bottle of ORFADIN oral suspension when you receive it, follow the instructions in “ How to prepare a bottle of ORFADIN oral suspension if the adapter is not inserted.”

If the adapter isinserted in your bottle of ORFADIN oral suspension when you receive it, follow the instructions in “ How to prepare a dose of ORFADIN oral suspension after the adapter is inserted.”

How to prepare a bottle of ORFADIN oral suspension if the adapter is not inserted:

See “ How should I store ORFADIN oral suspension?” for instructions on how to store ORFADIN oral suspension if the adapter is not inserted.

1. Remove the ORFADIN oral suspension bottle from the refrigerator 30 minutes to 1 hour before using it to allow it to reach room temperature.
  ORFADIN oral suspension should be thrown away (discarded) 60 days after it is removed from the refrigerator and the adapter is inserted in the bottle. Write the discard date on the bottle label.

1. Shake the bottle well for at least 20 secondsuntil the solid cake of particles at the bottom of the bottle is dissolved (See Figure B). Check that there are no particles left at the bottom of the bottle. Foam will form in the bottle.

Figure B

1. Remove the child resistant screw cap by pushing it down firmly and turning it counter-clockwise (See Figure C).

Figure C

1. Place the open bottle upright on a flat surface. Push the ribbed end of the adapter firmly into the neck of the bottle as far as it will go (See Figure D). Replace the child resistant screw cap on the bottle. Do not remove the adapter from the bottle after it is inserted.

Figure D

1. Follow the instructions in “ How to prepare a dose of ORFADIN oral suspension after the adapter is inserted.”

How to prepare a dose of ORFADIN oral suspension after the adapter is inserted

See “ How should I store ORFADIN oral suspension?” for instructions on how to store ORFADIN oral suspension after the adapter is inserted.

1. Shake the ORFADIN oral suspension bottle well for at least 5 seconds(See Figure E). Check that there are no particles left at the bottom of the bottle. Foam will form in the bottle.

Figure E

1. Remove the child resistant screw cap right away by pushing it down firmly and turning it counter-clockwise (See Figure F).

Figure F

1. Hold the oral syringe in one hand. With your other hand, fully push down (depress) the plunger (See Figure G).

Figure G

1. Keeping the bottle in an upright position, insert the oral syringe firmly into the adapter (See Figure H).

Figure H

1. Carefully turn the bottle upside down with the oral syringe in place (See Figure I). Wait until you can see that the foam is at the top of the bottle to avoid withdrawing bubbles into the syringe.

Figure I

1. Pull back slowly on the oral syringe plunger until the top edge of the black ring is at the line marking the dose prescribed by your healthcare provider (See Figure J). Figure J shows a dose of 1 mL as an example. If you see air bubbles in the oral syringe, fully push in the plunger so that the oral suspension flows back into the bottle. Then, withdraw your prescribed dose of oral suspension.

Figure J

1. Leave the oral syringe in the adapter and turn the bottle to an upright position. Place the bottle onto a flat surface. Remove the oral syringe by gently twisting it out of the bottle (See Figure K). Do not pull straight up on the syringe to remove it from the bottle because this can cause the adapter to come out of the bottle.

Figure K

1. Place the oral syringe in your mouth right away. Slowly push on the plunger until the oral syringe is empty. See Figure L).

Figure L

1. Leave the adapter in the bottle. Put the child resistant screw cap back on the bottle (See Figure M).

Figure M

1. Remove the plunger from the oral syringe barrel. Rinse the oral syringe with water after each use and let it air dry. Do not replace the plunger into the barrel of the oral syringe until ready to use again for your next dose to allow it to dry. Do not throw away the oral syringe.

- Talk to your healthcare provider or pharmacist if you have questions about how to use the oral syringe or if you lose the oral syringe.

How should I store ORFADIN oral suspension?

- Store the ORFADIN oral suspension bottle in an upright position. Keep the oral syringe with your medicine.

Before the adapter is inserted into the bottle:

- If the adapter has notbeen inserted into the bottle, store ORFADIN oral suspension in the refrigerator between 36°F to 46°F (2°C to 8°C).
- Do not freeze ORFADIN oral suspension.

After the adapter is inserted into the bottle:

- After the adapter has been inserted into the bottle, store ORFADIN oral suspension at room temperature, 77°F (25°C) or below.
- Throw away (discard) ORFADIN oral suspension 60 days after the adapter is inserted in the bottle. You or your pharmacist should write the discard date on the bottle label.

What are the ingredients in ORFADIN oral suspension?

Active ingredient:nitisinone

Inactive ingredients:hydroxypropyl methylcellulose, glycerol, polysorbate 80, sodium benzoate, citric acid monohydrate, trisodium citrate dihydrate, strawberry aroma (artificial) and purified water

This Instructions for Use has been approved by the U.S. Food and Drug Administration.

Manufactured by:
Apotek Produktion & Laboratorier AB, Sweden

Marketed by:
Sobi, Inc
77 Fourth Avenue, 3rdFloor, Waltham, MA 02451-7559

© Swedish Orphan Biovitrum AB (publ). All rights reserved.

Issued: 11/2021

Principal Display Panel - 4mg/ml Carton Label

Orfadin®
(nitisinone)

oral suspension
4 mg/ml

For Oral Use.

Rx only.

Shake well for 20 seconds before
first use. Shake well for 5 seconds
before each use.

90 ml

Principal Display Panel - 4mg/ml Vial Label

Orfadin®
(nitisinone)

oral suspension
4 mg/ml

Shake well before use.